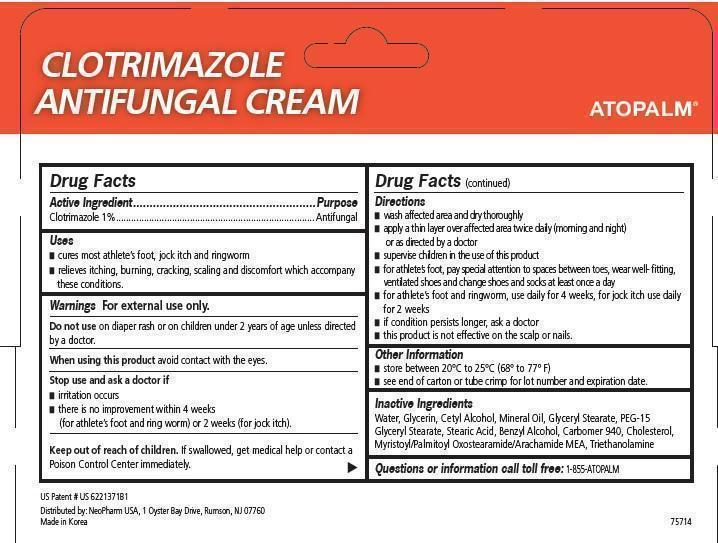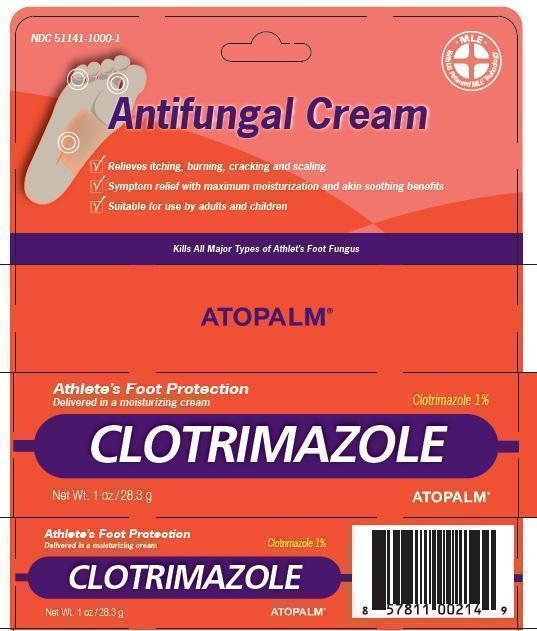 DRUG LABEL: ATOPALM CLOTRIMAZOLE ANTIFUNGAL 
                        
NDC: 51141-1000 | Form: CREAM
Manufacturer: NeoPharm Co., Ltd.
Category: otc | Type: HUMAN OTC DRUG LABEL
Date: 20150528

ACTIVE INGREDIENTS: CLOTRIMAZOLE 1 g/100 g
INACTIVE INGREDIENTS: WATER; GLYCERIN; CETYL ALCOHOL; MINERAL OIL; GLYCERYL MONOSTEARATE; STEARIC ACID; CARBOMER HOMOPOLYMER TYPE C; CHOLESTEROL; MYRISTOYL/PALMITOYL OXOSTEARAMIDE/ARACHAMIDE MEA; TROLAMINE

ATOPALM CLOTRIMAZOLE ANTIFUNGAL CREAM

Drug Facts

Active Ingredients

Clotrimazole 1%

Purpose

Antifungal

Uses

- cures most athlete's foot, jock itch and ringworm
- relieves itching, burning, cracking, scaling and discomfort which accompany these conditions.

Warnings For external use only.

Do not use on diaper rash or on children under 2 years of age unless directed by a doctor.

When using this product avoid contact with the eyes

Stop use and ask a doctor if

- irritation occurs
- there is no improvement within 4 weeks (for athlete's foot and ring worm) or 2 weeks (for jock itch).

Keep out of reach of children to avoid accidental ingestion. If swallowed, get medical help or contact a Poison Control Center immediately.

Directions

- wash affected area and dry thoroughly
- apply a thin layer over affected area twice daily (morning and night) or as directed by a doctor.
- supervise children in the use of this product
- for athlete's foot, pay special attention to spaces between toes, wear well-fitting, ventilated shoes and change shoes and socks at least once a day.
- for athlete's foot and ringworm, use daily for 4 weeks, for jock itch use daily for 2 weeks
- if condition persists longer, ask a doctor
- this product not effective on the scalp or nails

Other Information

- store at 20 degrees to 25 degrees (68 degrees to 77 degrees F)
- see end of carton or tube crimp for lot number and expiration date

Inactive Ingredients

Water, Glycerin,Cetyl Alcohol, Mineral Oil, Glyceryl Stearate, PEG Glyceryl Stearate, Stearic Acid, Benzyl Alcohol, Carbomer 940, Cholesterol, Myristoyl/Palmitoyl Oxostearamide/Arachamide MEA, Triethanolamine

Questions? Call 1-855-ATOPALM

US Patent US 6221371B1

Distributed by: NeoPharm Co., Ltd, 80 Wood Rd, 212 Camarillo, CA 93010

Made in Korea

Clotrimazole 1%
Antifungal
Cream